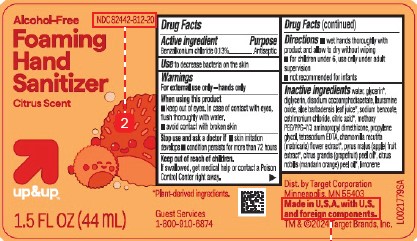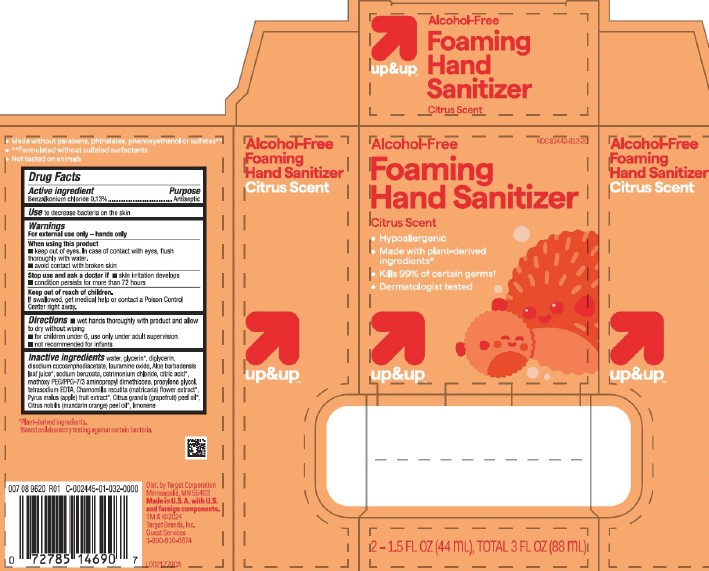 DRUG LABEL: Antiseptic Foaming Hand Sanitizer
NDC: 82442-812 | Form: LIQUID
Manufacturer: Target Corporation
Category: otc | Type: HUMAN OTC DRUG LABEL
Date: 20260218

ACTIVE INGREDIENTS: BENZALKONIUM CHLORIDE 1.3 mg/1 mL
INACTIVE INGREDIENTS: WATER; GLYCERIN; DIGLYCERIN; DISODIUM COCOAMPHODIACETATE; LAURAMINE OXIDE; ALOE VERA LEAF; SODIUM BENZOATE; CETRIMONIUM CHLORIDE; CITRIC ACID MONOHYDRATE; METHOXY PEG/PPG-7/3 AMINOPROPYL DIMETHICONE; PROPYLENE GLYCOL; EDETATE SODIUM; CHAMOMILE; APPLE; CITRUS MAXIMA FRUIT RIND OIL; MANDARIN OIL; LIMONENE, (+)-

Up & Up 812.000/812AA
Foaming Hand Sanitizer Alcohol Free

Claims

- Made without parabens, phthalates, phenoxyethanol or sulfates**
- **Formulated without sulfated surfactants
- Not tested on animals

Active ingredient

Benzalkonium chloride 0.13%

Purpose

Antiseptic

Use

- to decrease bacteria on the skin

Warnings

For external use only – hands only

When using this product

- keep out of eyes. In case of contact with eyes, flush thoroughly with water.
- avoid contact with broken skin

Stop use and ask a doctor if

- skin irritation develops
- condition persists for more than 72 hours

Keep out of reach of children.

If swallowed, get medical help or contact a Poison Control Center right away.

Directions

- wet hands thoroughly with product and allow to dry without wiping
- for children under 6, use only under adult supervision
- not recommended for infants

Inactive ingredients

water, glycerin*, diglycerin, disodium cocoamphodiacetate, lauramine oxide, Aloe barbadensis leaf juice*,
sodium benzoate, cetrimonium chloride, citric acid*, methoxy PEG/PPG-7/3 aminopropyl dimethicone, propylene glycol, tetrasodium EDTA, Chamomilla recutita (matricaria) flower extract*, Pyrus malus (apple) fruit extract*, Citrus grandis (grapefruit) peel oil*, Citrus nobilis (mandarin orange) peel oil*, limonene

Claims

*Plant-derived ingredients

†Based on laboratory testing against certain bacteria

Adverse Reaction

Dist. by Target Corporation

Minneapolis, MN 55403

Made in U.S.A. with U.S. and foreign components.

TM & ©2024

Target Brands, Inc.

Guest Services

1-800-910-6874

Principal display panel

NDC 82442-812-20

Alcohol-Free

Foaming Hand Sanitizer

Citrus Scent

- Hypoallergenic
- Made with plant-derived ingredients*
- Kills 99.9% certain germs†
- Dermatologist tested

up&up™

2-1.5 FL OZ (44 mL) TOTAL 3 FL OZ (88 mL)